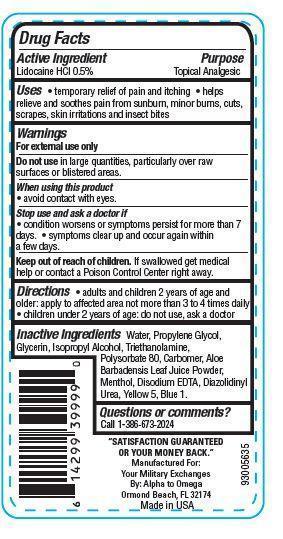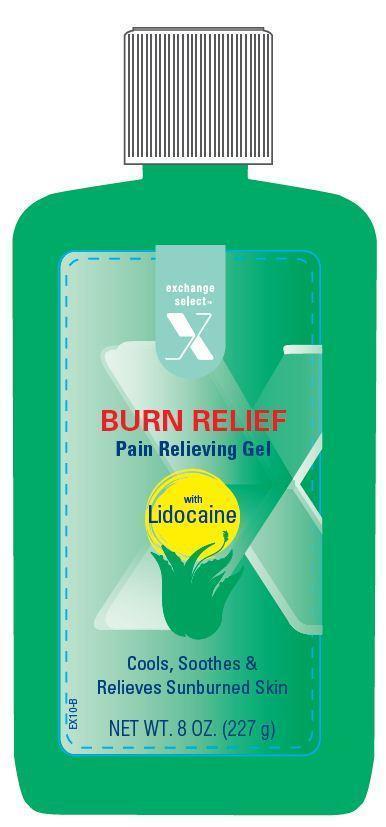 DRUG LABEL: Exchange Select Burn Relief
NDC: 55301-044 | Form: GEL
Manufacturer: ARMY AND AIR FORCE EXCHANGE SERVICE
Category: otc | Type: HUMAN OTC DRUG LABEL
Date: 20121115

ACTIVE INGREDIENTS: LIDOCAINE HYDROCHLORIDE 0.5 g/100 g
INACTIVE INGREDIENTS: WATER; TROLAMINE; ISOPROPYL ALCOHOL; EDETATE DISODIUM; ALOE VERA LEAF; PROPYLENE GLYCOL; GLYCERIN; POLYSORBATE 80; DIAZOLIDINYL UREA; MENTHOL

Drug Facts

Active Ingredient

Lidocaine HCl 0.50%

Purpose

Topical Analgesic

Uses

- temporary relief of pain and itching
- helps relieve and soothes pain from sunburn, minor burns, cuts, scrapes, skin irritations and insect bites

Warnings

For external use only

Do not use in large quantities, particularly over raw surfaces or blistered areas.

When using this product

- avoid contact with eyes.

stop use and ask a doctor if

- conditions worsens or symptoms persists for more than 7 days.
- symptoms clear up and occur again within a few days.

Keep out of reach of children.

If swallowed get medical help or contact a Poison Control Center right away.

Directions

- adults and children 2 years of age and older.apply to affected area not more than 3 to 4 times daily
- children under 2 years of age: do not use, ask a doctor.

Inactive Ingredients

Water, Propylene Glycol, Glycerin, Isopropyl Alcohol, Triethanolamine, Polysorbate 80, Carbomer, Aloe Barbadensis Leaf Juice Powder, Menthol, Disodium EDTA, Diazolidinyl Urea, Yellow 5, Blue 1.

Principal Display Panel

exchange

select

X

BURN RELIEF

Pain Relieving Gel

with
Lidocaine
Cools, Soothes and
Relieves Sunburned Skin
NET WT 8 OZ (227 g)